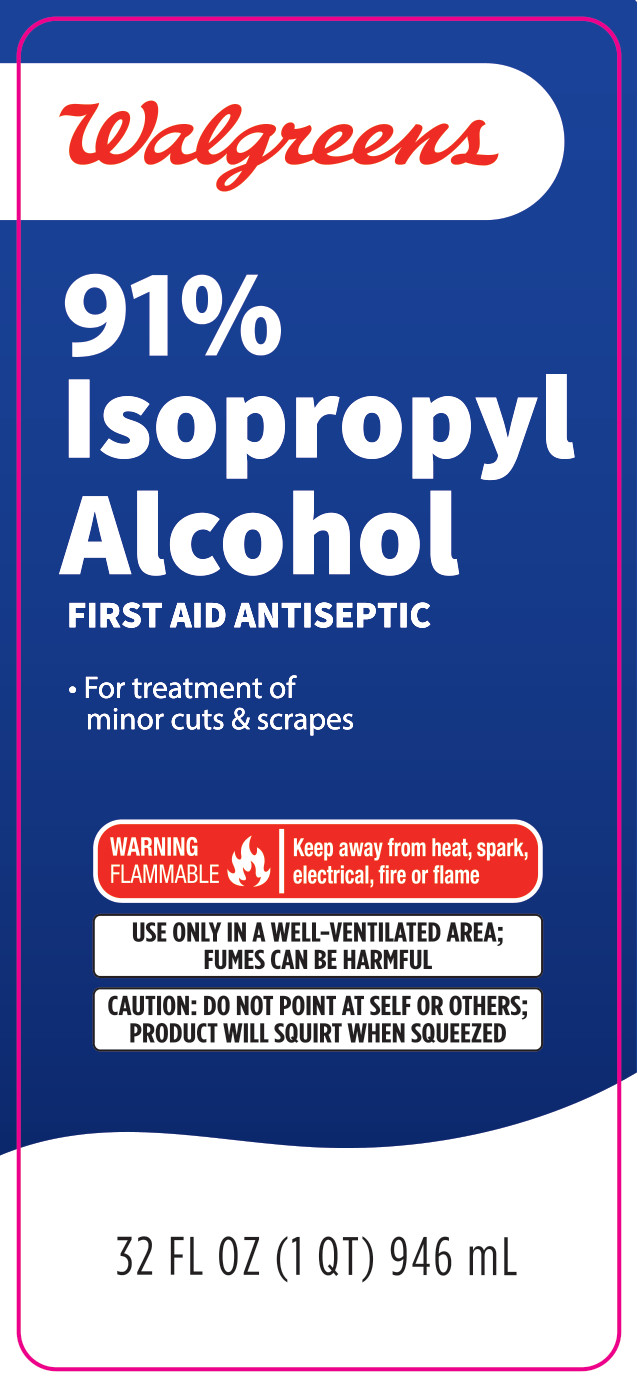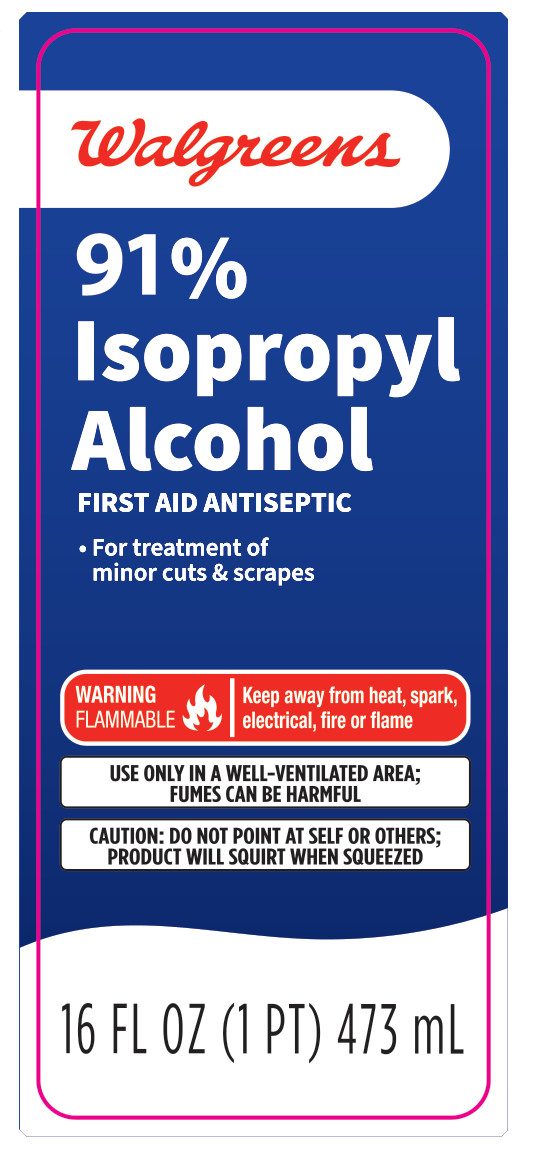 DRUG LABEL: Walgreens 91% Isopropyl Alcohol
NDC: 0363-0381 | Form: LIQUID
Manufacturer: Walgreens Co.
Category: otc | Type: HUMAN OTC DRUG LABEL
Date: 20250410

ACTIVE INGREDIENTS: ISOPROPYL ALCOHOL 0.91 mL/1 mL
INACTIVE INGREDIENTS: WATER

Walgreens 91% Isopropyl Alcohol

Active Ingredient

Isopropyl Alcohol 91%

Purpose

First aid antiseptic

Uses

first aid to help prevent the risk of infection in

- minor cuts
- scrapes
- burns

Warnings

For external use only.

- If taken internally serious gastric disturbances will result.

Flammable: Keep away from heat, spark, electrical, fire or flame

- Use only in well-ventilated area; funes may be toxic

Ask a doctor

before use if you have deep puncture wounds, animal bites or serious burns

When using this product

- do not get into eyes
- do not apply over large areas of the body
- do not use longer than one week

Stop use and ask a doctor if

condition persists or gets worse.

Keep out of reach of children.

If swallowed, get medical help or contact a Poison Control Center right away (1-800-222-1222).

Directions

- clean the affected area
- apply a small amount of this product on the area 1-3 times daily
- may be covered with a sterile bandage
- if bandaged, let dry first

Other information

- store at room temperature
- does not contain, nor is intended as a substitute for grain or ethyl alcohol

Inactive ingredient

water

Questions or comments?

1-800-925-4733

91% Isopropyl Alcohol - 32 fl oz

Walgreens

91% Isopropyl Alcohol

FIRST AID ANTISEPTIC

- For treatment of minor cuts & scrapes

WARNING

FLAMMABLE

Keep away from heat, spark, electricial, fire or flame

Use only in a well-ventilated area; fumes can be harmful

Caution: Do not point at self or others; product will squirt when squeezed

32 FL OZ (1 QT) 946 mL

91% Isopropyl Alcohol - 16 fl oz

Walgreens

91% Isopropyl Alcohol

FIRST AID ANTISEPTIC

- For treatment of minor cuts & scrapes

WARNING

FLAMMABLE

Keep away from heat, spark, electrical, fire or flame

Use only in a well-ventilated area; fumes can be harmful

Caution: Do not point at self or others; product will squirt when squeezed

16 FL OZ (1 PT) 473 mL